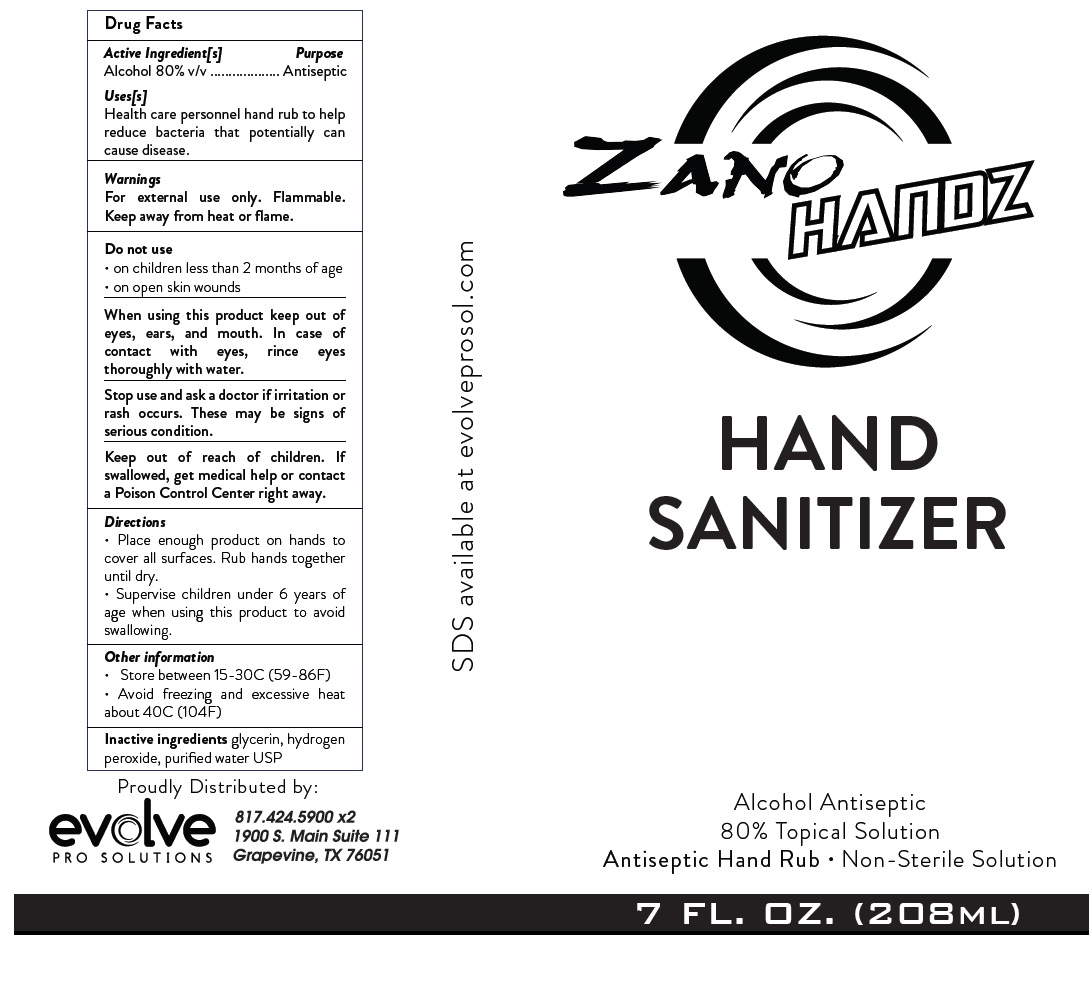 DRUG LABEL: ZANO HANDZ HAND SANITIZER
NDC: 74731-100 | Form: SOLUTION
Manufacturer: Evolve Pro Solutions, Inc.
Category: otc | Type: HUMAN OTC DRUG LABEL
Date: 20200707

ACTIVE INGREDIENTS: ALCOHOL 80 mL/100 mL
INACTIVE INGREDIENTS: GLYCERIN; HYDROGEN PEROXIDE; WATER

ZANO HANDZ HAND SANITIZER

Active Ingredient[s]

Alcohol 80% v/v

Purpose

Antiseptic

Use[s]

Health care personnel hand rub to help reduce bacteria that potentially can cause disease.

warnings

For external use only. Flammable. Keep away from heat or flame.

Do not use

- on children less than 2 months of age
- on open skin wounds

When using this product keep out of eyes, ears, and mouth. In case of contact with eyes, rinse eyes thoroughly with water.

Stop use and ask a doctor if irritation or rash occurs. These may be signs of serious condition.

Keep out of reach of children. If swallowed, get medical help or contact a Poison Control Center right away.

Directions

- Place enough product on hands to cover all surfaces. Rub hands together until dry.
- Supervise children under 6 years of age when using this product to avoid swallowing.

Other information

- Store between 15-30C (59-86F)
- Avoid freezing and excessive heat about 40C (104F)

Inactive ingredients

glycerin, hydrogen peroxide, purified water USP

Alcohol Antiseptic

80% Topical Solution

Antiseptic Hand Rub Non-sterile Solution

SDS available at evolveprosol.com

Proudly Distributed by:

evolve PRO SOLUTIONS

817.424.5900 x2

1900 S. Main Suite 111

Grapevine, TX 76051